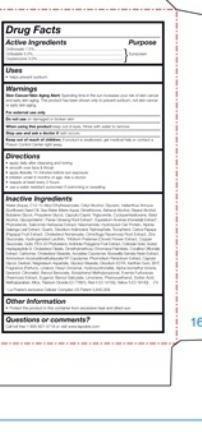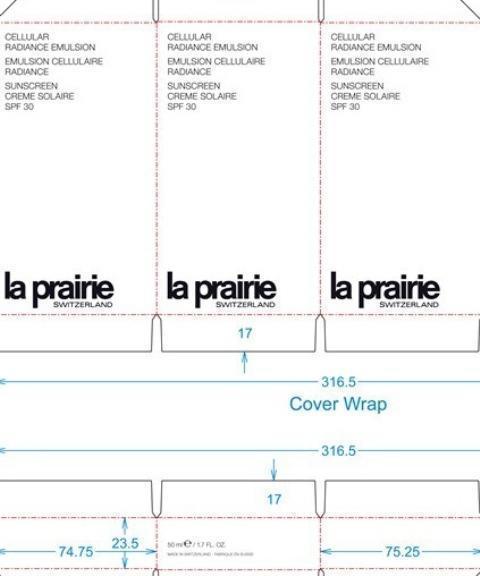 DRUG LABEL: Cellular Radiance Emulsion SPF 30
NDC: 68807-320 | Form: CREAM
Manufacturer: Temmentec Ag
Category: otc | Type: HUMAN OTC DRUG LABEL
Date: 20170103

ACTIVE INGREDIENTS: AVOBENZONE 75 mg/100 kg; OCTINOXATE 50 mg/100 kg; OCTISALATE 30 mg/100 kg
INACTIVE INGREDIENTS: WATER; CETYL ALCOHOL; GLYCERIN; SUNFLOWER OIL; DIMETHICONE; DOCOSANOL; STEARYL ALCOHOL; BUTYLENE GLYCOL; PROPYLENE GLYCOL; MEDIUM-CHAIN TRIGLYCERIDES; CYCLOMETHICONE 5; BATILOL; ASIAN GINSENG; EQUISETUM ARVENSE BRANCH; SALICORNIA EUROPAEA; NIACINAMIDE; ALPINIA GALANGA LEAF; SILICON DIOXIDE; ADENOSINE TRIPHOSPHATE DISODIUM; TOCOPHEROL; PAPAYA; CHOLESTERYL NONANOATE; BLACK COHOSH; ZINC GLUCONATE; TRIFOLIUM PRATENSE FLOWER; COPPER GLUCONATE; ACTINIDIA POLYGAMA FRUIT; GOLD; CHOLESTERYL OLEATE; CORALLINA OFFICINALIS; CARBOMER 934; CHOLESTERYL STEARATE; INDIAN FRANKINCENSE; AMMONIUM ACRYLOYLDIMETHYLTAURATE/VP COPOLYMER; PHORMIDIUM PERSICINUM; CAPRYLYL GLYCOL; DEXTRAN 1; MAGNESIUM ASPARTATE; GLYCERYL MONOSTEARATE; EDETATE DISODIUM; XANTHAN GUM; BUTYLATED HYDROXYTOLUENE; LINALOOL, (+)-; .ALPHA.-HEXYLCINNAMALDEHYDE; HYDROXYCITRONELLAL; ISOMETHYL-.ALPHA.-IONONE; GERANIOL; .BETA.-CITRONELLOL, (R)-; BENZYL BENZOATE; BUTYLPHENYL METHYLPROPIONAL; PSEUDEVERNIA FURFURACEA; EUGENOL; BENZYL SALICYLATE; LIMONENE, (-)-; PHENOXYETHANOL; SORBIC ACID; METHYLPARABEN; MICA; TITANIUM DIOXIDE; FD&C RED NO. 4; FD&C YELLOW NO. 5

Cellular Radiance Emulsion SPF 30

Active Ingredients Purpose

Octinoxate 7.5% Sunscreen

Octisalate 5.0% Sunscreen

Oxybenzone 3.0% Sunscreen

Uses

helps prevent sunburn

Keep out of reach of children. If swallowed, get medical help or contact a Poison Control Center right away.

Stop use and ask a doctor if rash occurs

WARNINGS

Skin Cancer/Skin Aging Alert: Spending time in the sun increases your risk of skin cancer and early skin aging. This product has been shown only to prevent sunburn, not skin cancer or early skin aging.

For external use only

Do not use on damaged or broken skin

When using this product keep out of eyes. Rinse with water to remove.

Directions

apply daily after cleansing and toning

smooth over face and throat

apply liberally 15 minutes before sun exposure

children under 6 months of age: Ask a doctor

reapply at least every 2 hours

use a water resistant sunscreen if swimming or sweating

Inactive Ingredients:

Water (Aqua), C12-15 Alkyl Ethylhexanoate, Cetyl Alcohol, Glycerin, Helianthus Annuus (Sunflower) Seed Oil, Sea Water (Maris Aqua), Dimethicone, Behenyl Alcohol, Stearyl Alcohol, Butylene Glycol, Propylene Glycol, Caprylic/Capric Triglyceride, Cyclopentasiloxane, Batyl Alcohol, Glycoproteins, Panax Ginseng Root Extract, Equisetum Arvense (Horsetail) Extract, Phytosterols,
Salicornia Herbacea Extract, Niacinamide, Hydrolyzed Oat Protein, Alpinia Galanga Leaf Extract, Quartz,
Disodium Adenosine Triphosphate,Tocopherol, Carica Papaya (Papaya) Fruit Extract, Cholesteryl Nonanoate,
Cimicifuga Racemosa Root Extract, Zinc Gluconate, Hydrogenated Lecithin, Trifolium Pratense (Clover) Flower Extract, Copper Gluconate, Gold, PEG-20 Phytosterol, Actinidia Polygama Fruit Extract, Acetyl Heptapeptide, Colloidal Gold, Cholesteryl Oleate, Dimethylmethoxy Chromanyl Palmitate, Corallina Officinalis Extract, Carbomer, Cholsteryl Stearate, Acrylates Copolymer, Boswellia Serrata Resin Extract, Ammonium Acryloyldimethltaurate/VP Copolymer, Phormidium Persicinum Extract, Caprylyl Glycol, Dextran, Magnesium Asparate, Glyceryl Stearate, Disodium EDTA, Xanthan Gum, BHT, Fragrance (Parfum), Linalool, Hexyl Cinnamal, Hydroxycitronellal, Alpha-Isomethyl Ionone, Geraniol, Citronellol, Benzyl Benzoate, Butylphenyl Methylpropional, Evernia Furfuracea (Treemoss) Extract, Eugenol, Benzyl Salicylate, Limonene, Phenoxyethanol, Sorbic Acid, Methylparaben, Mica, Titanium Dioxide (CI 77891), Red (CI 14700), Yellow 5 (CI 19140)

PACKAGE LABEL

Cellular Radiance Emulsion

Emulsion Cellulaire Radiance

Sunscreen Creme Solaire

SPF 30

La Prairie Switzerland

50 ml/ 1.7 Fl. Oz.